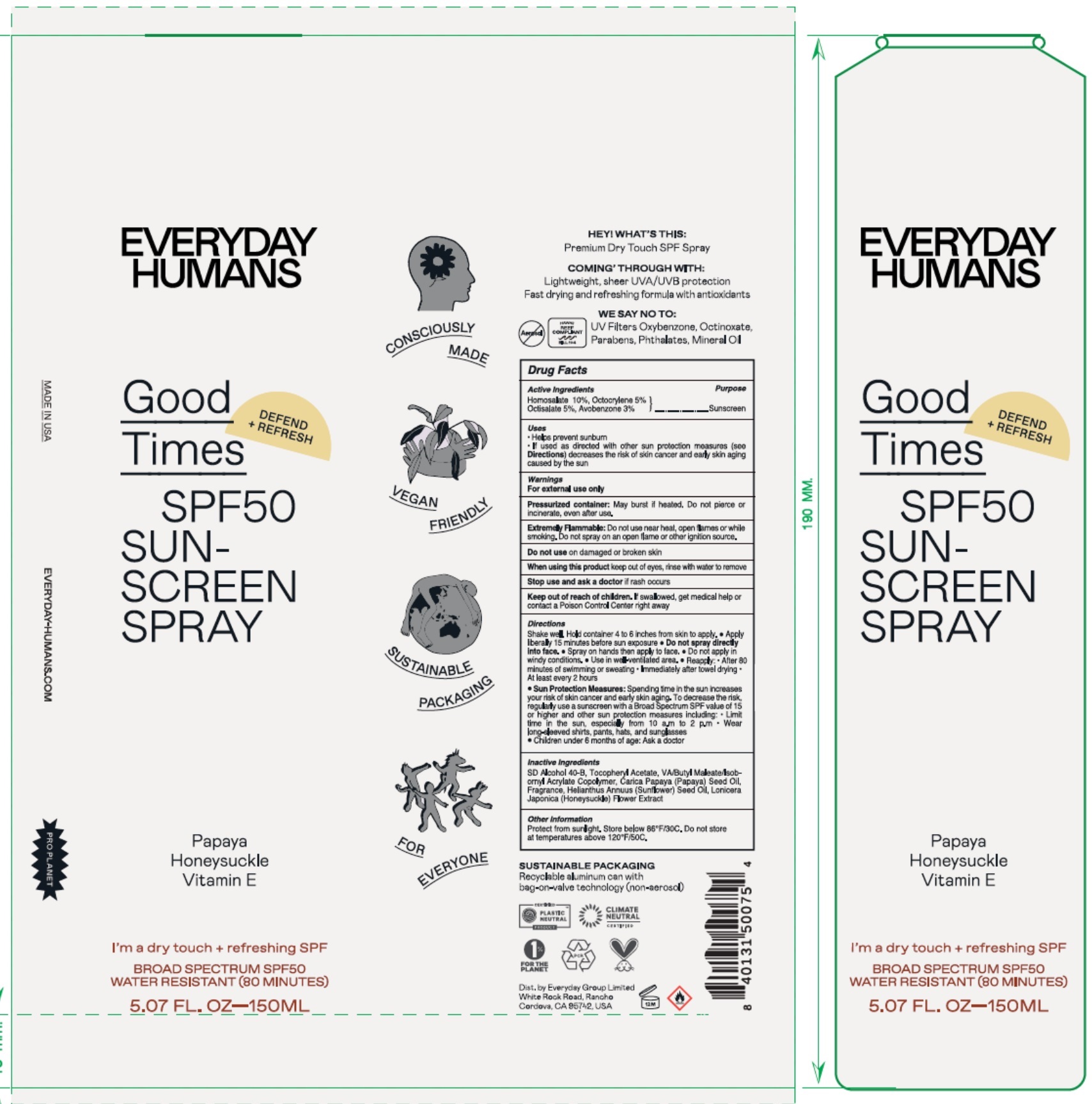 DRUG LABEL: Good Times SPF 50 Sunscreen
NDC: 72098-009 | Form: SPRAY
Manufacturer: EVERYDAY GROUP LIMITED
Category: otc | Type: HUMAN OTC DRUG LABEL
Date: 20251204

ACTIVE INGREDIENTS: HOMOSALATE 100 mg/1 mL; OCTOCRYLENE 50 mg/1 mL; OCTISALATE 50 mg/1 mL; AVOBENZONE 30 mg/1 mL
INACTIVE INGREDIENTS: DIBUTYL MALEATE; PAPAYA SEED OIL; SUNFLOWER OIL; LONICERA JAPONICA FLOWER; .ALPHA.-TOCOPHEROL ACETATE

Good Times SPF 50 Sunscreen Spray

Active ingredients

Homosalate 10% Octocrylene 5% Octisalate 5% Avobenzone 3%

Purpose

Sunscreen

Uses

- Helps prevent sunburn
- if used as directed with other sun protection measures (see) decreases the risk of skin cancer and early skin aging caused by the sun Directions

Warnings

For external use only

May burst if heated. Do not pierce or incinerate, even after use. Pressurized container:

Do not use near heal, open flames or while smoking. Do not spray on an open flame or other ignition source. Extermely Flammable:

Do not use

on damaged or broken skin

When using this product

keep out of eyes, rinse with water to remove

Stop use and ask a doctor

if rash occurs

Keep out of reach of children.

If swallowed, get medical help or contact a Poison Control Center right away

Directions

Shake well. Hold container 4 to 6 inches from skin to apply. • Apply liberally 15 minutes before sun exposure • • Spray on hands then apply to face. • Do not apply in windy conditions. • Use in well-ventilated area. • Reapply: • After 80 minutes of swimming or sweating • Immediately after towel drying • At least every 2 hours • Spending time in the sun increases your risk of skin cancer and early skin aging. To decrease the risk, regularly use a sunscreen with a Broad Spectrum SPF value of 15 or higher and other sun protection measures including: Limit time in the sun, especially from 10 a.m. to 2 p.m. • Wear long-sleeved shirts, pants, hats, and sunglasses • Children under 6 months of age: Ask a doctor Do not spray directly into face. Sun Protection Measures:

Inactive ingredients

SD Alcohol 40-B, Tocopheryl Acetate, VA/Butyl Maleate/Isobornyl Acrylate Copolymer, Carica Papaya (Papaya) Seed Oil, Fragrance, Helianthus Annuus (Sunflower) Seed Oil, Lonicera Japonica (Honeysuckle) Flower Extract

Other information

Protect from sunlight. Store below 86°F/30°C. Do not store at temperatures above 120°F/50C.